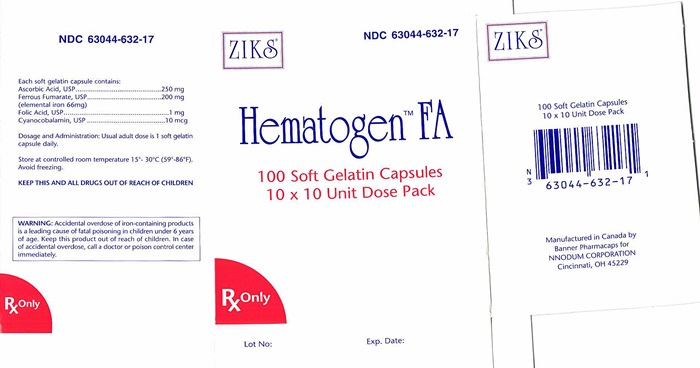 DRUG LABEL: Hematogen FA
                
                
                
                
                
                
                
NDC: 63044-632 | Form: CAPSULE
Manufacturer: Nnodum Pharmaceuticals
Category: prescription | Type: HUMAN PRESCRIPTION DRUG LABEL
Date: 20241228

ACTIVE INGREDIENTS: FERROUS FUMARATE 66 mg/1 1; ASCORBIC ACID 250 mg/1 1; FOLIC ACID 1 mg/1 1; CYANOCOBALAMIN 10 ug/1 1

Hematogen FA

DESCRIPTION

CONTENTS : Each maroon and brown soft gelatin capsule contains:

Ferrous fumarate ........................................................................200 mg

(66 mg elemental iron)

Ascorbic acid ..............................................................................250 mg

Folic acid ........................................................................................1 mg

Cyanocobalamin .........................................................................10 mcg

DISCUSSION : The amount of elemental iron and the absorption of the iron components of commercial iron preparations vary widely. It is further established that certain "accessory components" may be included to enhance absorption and utilization of iron. Hematogen FA Capsules are formulated to provide the essential factors for a complete, versatile hematinic.

ACTIONS

HIGH ELEMENTAL IRON CONTENT: Ferrous fumarate, used in Hematogen FA Capsules, is an organic iron 1,2 complex which has the highest elemental iron content of any hematinic salt - 33% This compares with 20% for ferrous sulfate (heptahydrate) and 13% for ferrous gluconate.

MORE COMPLETE ABSORPTION: It has been repeatedly shown that Ascorbic acid, when given in sufficient amounts, can increase the absorption of ferrous Iron from the gastrointestinal tract. The absorption promoting effect is mainly due to the reducing action of ascorbic acid within the gastrointestinal lumen, which helps to prevent or delay the formation of insoluble or less dissociated ferric compounds. Iron absorption has been shown to increase sharply with increasing amounts of ascorbic acid, showing a gain in absorption of approximately 40% at 250 mg. Above 250 mg, the gain becomes insignificant, with an additional gain of only approximately 8% at 500 mg. Each Hematogen FA capsule contains 250 mg of ascorbic acid, believed to be the optimal amount

PROMOTES MOVEMENT OF PLASMA IRON: Ascorbic acid also plays an important role in the movement of plasma iron to storage depots in the tissues .The action, which leads to the transport of plasma iron to ferritin, presumably involves its reducing effect, converting transferrin iron from the ferric to the ferrous state. There is also evidence that ascorbic acid improves iron utilization, presumably as a further result of its reducing action and some evidence that effect upon erythropoiesis. Ascorbic acid is further alleged to enhance the conversion of folic acid to a more physiologically active form, folinic acid, which would make it even more important in the treatment of anemia since it would aid in the utilization of dietary folic acid."

EXCELLENT ORAL TOLERATION: Ferrous fumarate is used in Hematogen FA Capsules because it is less likely to cause the gastric disturbances so often associated with oral iron therapy. Ferrous fumarate has a low ionization constant and high solubility in the entire pH range of the gastrointestinal tract. It does not precipitate proteins or have the astringency of more ionizable forms of iron, and does not interfere with proteolytic or diastatic activities of the digestive system. Because of excellent oral toleration, Hematogen FA Capsules can usually be administered between meals when iron absorption is maximal.

FOLIC ACID SUPPLEMENTATION: The use of supplemental folic acid may be indicated in patients with increased requirements for this vitamin, such as iron deficiency anemia. Folic acid administration may 12 reduce the risk of neural tube defects in the developing fetus . Folic acid has also been shown to reduce circulating homocysteine leveIs in the blood . FoIate as 5-methyltetrahydrofolate and B as methylcobalamin are involved in the remethylation reaction of homocysteine to methionine. Elevated homocysteine plasma levels are associated with increased risk of preeclampsia, neural tube defects, myocardial infarction and artherosclerosis.

TOXICITY: Ferrous fumarate was found to be the least toxic of three popular oral iron salts, with an oral LD of 630 mg/kg. In the same report, the LD of ferrous gluconate was reported to be 320 mg/kg and ferrous sulfate 230 mg/kg.

INDICATIONS

For the treatment of all anemias responsive to oral iron therapy, such as hypochromic anemia associated with pregnancy, chronic or acute blood loss, dietary restriction, metabolic disease and post-surgical convalescence.

CONTRAINDICATIONS

Hemochromatosis and hemosiderosis are contraindications to iron therapy. Folic acid is contraindicated in patients with pernicious anemia (see PRECAUTIONS).

WARNING

WARNING: Accidental overdose of iron-containing products is a leading cause of fatal poisoning in children under 6 years of age. Keep this product out of reach of children. In case of accidental overdose, call a doctor or poison control center immediately.

PRECAUTIONS

Folic acid should not be prescribed until the diagnosis of pernicious anemia has been eliminated, since it can 14 alleviate the hematologic manifestations, while allowing neurological damage to continue undetected.

ADVERSE REACTIONS

Average capsule doses in sensitive individuals or excessive dosage may cause nausea, skin rash, vomiting, diarrhea, precordial pain, or flushing of the face and extremities.

DOSAGE AND ADMINISTRATION

Usual adult dose is 1 soft gelatin capsule daily.

HOW SUPPLIED

Capsules NDC 63044-632-17, Unit Dose Box 100

CAUTION: Federal law prohibits dispensing without prescription.

Manufactured by:

Catalent Australia PTY LTD

Distributed by:

Nnodum Pharmaceuticals

Cincinnati, Ohio 45240

BIBILOGRAPHY

'Berk, M.S. and Novich, M.A.: 'Treatment of Iron Deficiency Anemia With Ferrous Fumarate," Am. J. Obst. & Gynec., 203-206, 1962. 'Shapleigh, J.B., and Monigomery, A.:Am. Pract. & Dig. Treat. 1 Q-461 , 1959. 3 Brise, H. and Hallberg, L.: "Effect of Ascorbic Acid on Iron Absorption," Acta. Med Scand.171:376,51-58,1962. 4 ‘New Drugs, p. 309, AMA, Chicago, 1966. 5 'Mazur, A., Green, S. and Carleton, A,: "Mechanism of Plasma Iron Incorporation into Hepatic Ferritin," J. Bio. Chern. 3:595-603, 1960. 'Greenberg, S.M, Tucker, A. E., Mathues, Hand JD: "Iron Absorption and Metabolism, I. Interrelationship of Ascorbic Acid and Vitamin E," J. Nutrition 6319:31,}957 'Moore, C.V and Dubach, R "Observatiol).S"9!)tl\§~rJ1~P?f Iron fromFoodsTag~edv-:ith ~ron frans. A~. f'hysic.64:~1.~, ~ ~uDac1i, R. and-MoOte, C V Studies in Iron Transportation and Metabolism, "Arch. Int. Med 95:181,1955. 'Gorten, M K. and Bradley, J E.: "The Treatment of Nutritional Anemia in Infancy and Childhood with Oral Iron and Ascorbic Acid," J Pediatrics, 45:1, 1954. ,oMazur, A.: "Role of Ascorbic Acid in the Incorporation of Plasma Iron into Ferritin," Ann. N.Y. Acad. Sci, 92:223-229, .1961. I'COX, E.V. et al.: 'The Anemia of Scurvy," Amer. J. Med 42:220-227,1967. "McEvoy, G.K., Ed.: AHFS Drug Information, p. 2667-2669, Am. Soc. Hosp. Pharm., Bethesda, 1996. '3Berenbaum, M.C. et al.: Blood, 15:540, 1960. "Dru~ Information for the Health Care Professional, p.1365-1368, U S Phar- macopeial Conven., Rockville, 1995. Franken DG, Boers GH, Blom HJ, Trijbels JM "Effect of various regi- mens of vitamin B, and folic acid on mild hyperhomocystelnemia in vascular patients." J Inherit. Metab. Dis 1994; 17:159-62. "Brattstrom L, Israeisson B, Norrving B, et al. "Impaired homocysteine metabolism in early- onset cerebral and peripheral occlusive disease - effects 01 pyridoxine and folic acid treatment." Atheroscle- rosi~ 1990; 812004-6. "Ka'1!J S. Wong PWK, NoruslS-t.x:"Homocysteinemla due_to folate deficiency." Me- tabolism~9$1!"4S8-62. ,~ BH.SI8w..-SO';Savage DG, Lindernbaum J. "Dia9nosis of cobalamin deficiency. "IL usefulness of serum methylmalonic acid and total homocysteine concentrations. Am J. Hema- 1011990; 34 90-98. '"Dekker GA, de Vries JI, Doelitzsch PM, Huijgens PC, von Blomberg BM, Jakobs, C, van Geijn HP 1985 "Underj:ging disorder associated with severe early-onset preeclampsia." Am. J. Obstet. Gy- necol. 173: 1042-1046. Mills JL, McPartlin JM, Kirke PN, Lee Y J, Conley MR, Weir DG, Scott JM 1995. "Ho-mocysteine metabolism in pregnancies complicated by neural-tube defects." Lancet. 345: 149-151. " Steegers- Theunissen RP, Boers GH, Blom HJ, Nijhuis JG, Thomas CM, Borm GF, Eskes TK. 1995. "Neural tube defects and elevated homocysteine levels in amniotic fluid." Am. J. Obstel Gynecol172 1436-1441. "Landgren F. Is- raelsson B, Lindgren A, Hultberg B, Andersson A, Brattstrom L 1995. "Plasma homocysteine in acute my- ocardial infarction: Homocysteine-lowering effect of folic acid." J. Intern. Med. 237: 381-388. '3Mayer EL, Ja- cobsen DW, Robinson K. 1996. "Homocysteine and Coronary Atherosclerosis." J.Am. Coli. Cardiol27: 517-27.